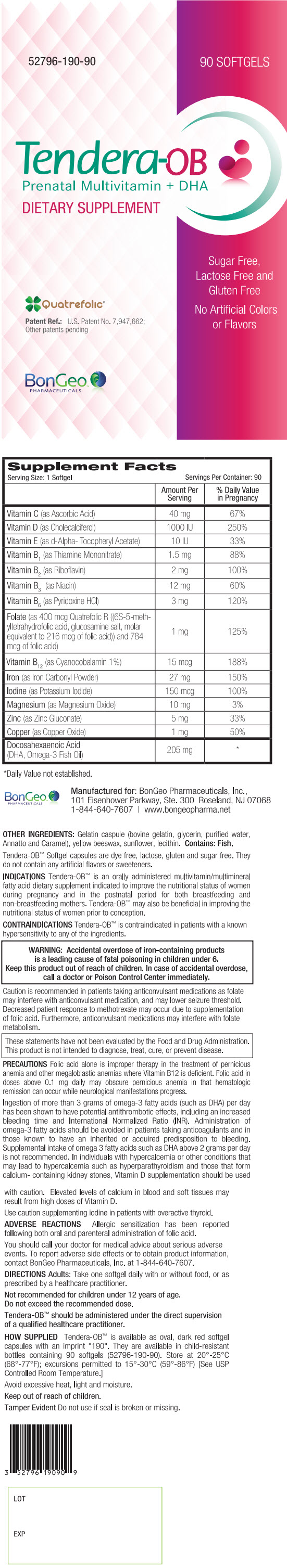 DRUG LABEL: Tendera-OB
NDC: 52796-190 | Form: CAPSULE
Manufacturer: BonGeo Pharmaceuticals, Inc.
Category: other | Type: DIETARY SUPPLEMENT
Date: 20190319

ACTIVE INGREDIENTS: ASCORBIC ACID 40 mg/1 1; CHOLECALCIFEROL 1000 [iU]/1 1; .ALPHA.-TOCOPHEROL 10 [iU]/1 1; THIAMINE MONONITRATE 1.5 mg/1 1; RIBOFLAVIN 2 mg/1 1; NIACIN 12 mg/1 1; PYRIDOXINE HYDROCHLORIDE 3 mg/1 1; LEVOMEFOLATE GLUCOSAMINE 1 mg/1 1; CYANOCOBALAMIN 15 ug/1 1; IRON PENTACARBONYL 27 mg/1 1; POTASSIUM IODIDE 150 ug/1 1; MAGNESIUM OXIDE 10 mg/1 1; ZINC GLUCONATE 5 mg/1 1; CUPRIC OXIDE 1 mg/1 1; DOCONEXENT 205 mg/1 1
INACTIVE INGREDIENTS: glycerin; water; annatto; caramel; yellow wax; helianthus annuus whole; fish, unspecified

Tendera-OB Prenatal Multivitamin + DHA

STATEMENT OF IDENTITY

Supplement Facts
Serving Size: 1 Softgel | Servings Per Container: 90
 | Amount Per Serving | % Daily Value in Pregnancy
Vitamin C (as Ascorbic Acid) | 40 mg | 67%
Vitamin D (as Cholecalciferol) | 1000 IU | 250%
Vitamin E (as d-Alpha- Tocopheryl Acetate) | 10 IU | 33%
Vitamin B1 (as Thiamine Mononitrate) | 1.5 mg | 88%
Vitamin B2 (as Riboflavin) | 2 mg | 100%
Vitamin B3 (as Niacin) | 12 mg | 60%
Vitamin B6 (as Pyridoxine HCl) | 3 mg | 120%
Folate (as 400 mcg Quatrefolic R ((6S-5-meth-yltetrahydrofolic acid, glucosamine salt, molar equivalent to 216 mcg of folic acid)) and 784 mcg of folic acid) | 1 mg | 125%
Vitamin B12 (as Cyanocobalamin 1%) | 15 mcg | 188%
Iron (as Iron Carbonyl Powder) | 27 mg | 150%
Iodine (as Potassium Iodide) | 150 mcg | 100%
Magnesium (as Magnesium Oxide) | 10 mg | 3%
Zinc (as Zinc Gluconate) | 5 mg | 33%
Copper (as Copper Oxide) | 1 mg | 50%
Docosahexaenoic Acid (DHA, Omega-3 Fish Oil) | 205 mg | [Daily Value not established.]

OTHER INGREDIENTS: Gelatin capsule (bovine gelatin, glycerin, purified water, Annatto and Caramel), yellow beeswax, sunflower, lecithin. Contains: Fish.

Tendera-OB™ Softgel capsules are dye free, lactose, gluten and sugar free. They do not contain any artificial flavors or sweeteners.

INDICATIONS

Tendera-OB™ is an orally administered multivitamin/multimineral fatty acid dietary supplement indicated to improve the nutritional status of women during pregnancy and in the postnatal period for both breastfeeding and non-breastfeeding mothers. Tendera-OB™ may also be beneficial in improving the nutritional status of women prior to conception.

CONTRAINDICATIONS

Tendera-OB™ is contraindicated in patients with a known hypersensitivity to any of the ingredients.

WARNINGS

WARNING: Accidental overdose of iron-containing products is a leading cause of fatal poisoning in children under 6.
Keep this product out of reach of children. In case of accidental overdose, call a doctor or Poison Control Center immediately.

HEALTH CLAIM

Caution is recommended in patients taking anticonvulsant medications as folate may interfere with anticonvulsant medication, and may lower seizure threshold. Decreased patient response to methotrexate may occur due to supplementation of folic acid. Furthermore, anticonvulsant medications may interfere with folate metabolism.

HEALTH CLAIM

These statements have not been evaluated by the Food and Drug Administration. This product is not intended to diagnose, treat, cure, or prevent disease.

PRECAUTIONS

Folic acid alone is improper therapy in the treatment of pernicious anemia and other megaloblastic anemias where Vitamin B12 is deficient. Folic acid in doses above 0.1 mg daily may obscure pernicious anemia in that hematologic remission can occur while neurological manifestations progress.

Ingestion of more than 3 grams of omega-3 fatty acids (such as DHA) per day has been shown to have potential antithrombotic effects, including an increased bleeding time and International Normalized Ratio (INR). Administration of omega-3 fatty acids should be avoided in patients taking anticoagulants and in those known to have an inherited or acquired predisposition to bleeding. Supplemental intake of omega 3 fatty acids such as DHA above 2 grams per day is not recommended. In individuals with hypercalcemia or other conditions that may lead to hypercalcemia such as hyperparathyroidism and those that form calcium- containing kidney stones, Vitamin D supplementation should be used with caution. Elevated levels of calcium in blood and soft tissues may result from high doses of Vitamin D.

Use caution supplementing iodine in patients with overactive thyroid.

ADVERSE REACTIONS

Allergic sensitization has been reported following both oral and parenteral administration of folic acid.

You should call your doctor for medical advice about serious adverse events. To report adverse side effects or to obtain product information, contact BonGeo Pharmaceuticals, Inc. at 1-844-640-7607.

DIRECTIONS

Adults

Take one softgel daily with or without food, or as prescribed by a healthcare practitioner.

HEALTH CLAIM

Not recommended for children under 12 years of age.

Do not exceed the recommended dose.

Tendera-OB™ should be administered under the direct supervision of a qualified healthcare practitioner.

HOW SUPPLIED

Tendera-OB™ is available as oval, dark red softgel capsules with an imprint "190". They are available in child-resistant bottles containing 90 softgels (52796-190-90). Store at 20°-25°C (68°-77°F); excursions permitted to 15°-30°C (59°-86°F) [See USP Controlled Room Temperature.]

Avoid excessive heat, light and moisture.

Keep out of reach of children.

Tamper Evident

Do not use if seal is broken or missing.

HEALTH CLAIM

LOT

EXP

HEALTH CLAIM

Manufactured for: BonGeo Pharmaceuticals, Inc.,
101 Eisenhower Parkway, Ste. 300 Roseland, NJ 07068
1-844-640-7607 | www.bongeopharma.net

PRINCIPAL DISPLAY PANEL - 90 Softgel Bottle Label

52796-190-90
90 SOFTGELS

Tendera-OB
Prenatal Multivitamin + DHA
DIETARY SUPPLEMENT

Quatrefolic®
Patent Ref.: U.S. Patent No. 7,947,662;
Other patents pending

Sugar Free,
Lactose Free and
Gluten Free

No Artificial Colors
or Flavors

BonGeo™
PHARMACEUTICALS